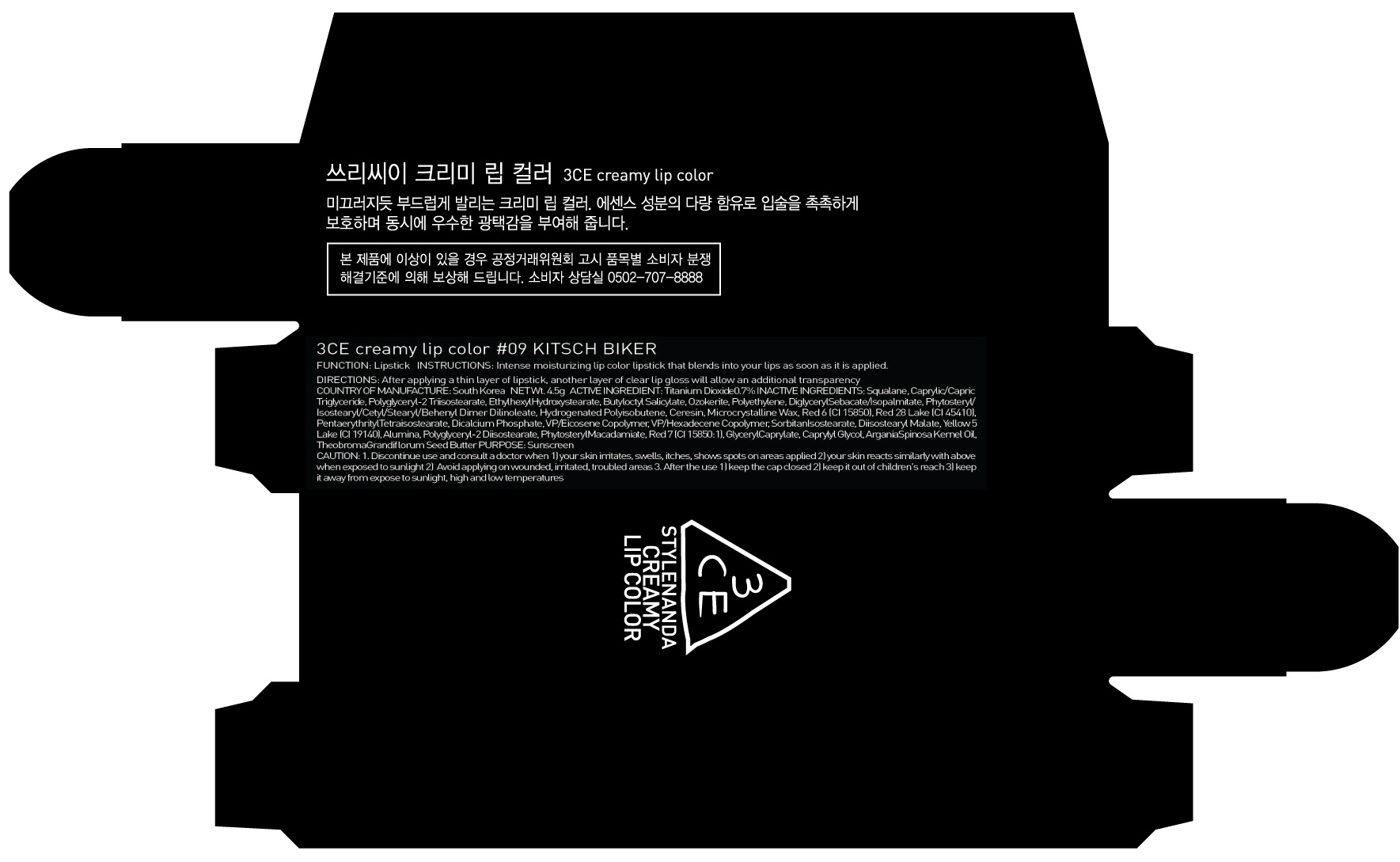 DRUG LABEL: 3CE CRE AMY LIP COLOR 09 KI TSCH BIKER
NDC: 60764-118 | Form: LIPSTICK
Manufacturer: Nanda Co., Ltd
Category: otc | Type: HUMAN OTC DRUG LABEL
Date: 20161014

ACTIVE INGREDIENTS: Titanium Dioxide 0.03 g/4.5 g
INACTIVE INGREDIENTS: Squalane; Ethylhexyl Hydroxystearate

ACTIVE INGREDIENT

Active Ingredient: Titanium Dioxide 0.7%

INACTIVE INGREDIENT

Inactive Ingredients: Squalane, Caprylic/Capric Triglyceride, Polyglyceryl-2 Triisostearate, Ethylhexyl Hydroxystearate, Butyloctyl Salicylate, Ozokerite, Polyethylene, DiglycerylSebacate/Isopalmitate, Phytosteryl/Isostearyl/Cetyl/Stearyl/Behenyl Dimer Dilinoleate, Hydrogenated Polyisobutene, Ceresin, Microcrystalline Wax, Red 6 (CI 15850), Red 28 Lake (CI 45410), PentaerythritylTetraisostearate, Dicalcium Phosphate, VP/Eicosene Copolymer, VP/Hexadecene Copolymer, SorbitanIsostearate, Diisostearyl Malate, Yellow 5 Lake (CI 19140), Alumina, Polyglyceryl-2 Diisostearate, Phytosteryl Macadamiate, Red 7 (CI 15850:1), GlycerylCaprylate, Caprylyl Glycol, ArganiaSpinosa Kernel Oil, Theobroma Grandiflorum Seed Butter

PURPOSE

Purpose: Sunscreen

CAUTION

CAUTION: 1. Discontinue use and consult a doctor when - your skin irritates, swells, itches, shows spots on areas applied - your skin reacts similarly with above when exposed to sunlight 2. Avoid applying on wounded, irritated, troubled areas 3. After the use - keep the cap closed - keep it out of children's reach - keep it away from expose to sunlight, high and low temperatures

DESCRIPTION

INSTRUCTIONS: Intense moisturizing lip color lipstick that blends into your lips as soon as it is applied.

Directions: After applying a thin layer of lipstick, another layer of clear lip gloss will allow an additional transparency